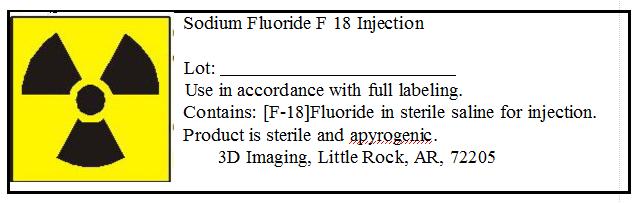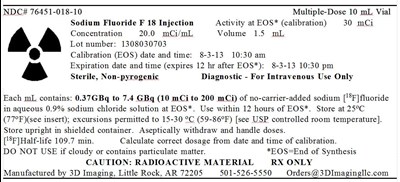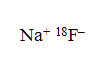 DRUG LABEL: Sodium Fluoride				
NDC: 76451-018 | Form: INJECTION
Manufacturer: 3D Imaging Drug Design and Development LLC
Category: prescription | Type: HUMAN PRESCRIPTION DRUG LABEL
Date: 20260107

ACTIVE INGREDIENTS: SODIUM FLUORIDE F-18 200 mCi/1 mL
INACTIVE INGREDIENTS: SODIUM CHLORIDE 9 mg/1 mL

HIGHLIGHTS OF PRESCRIBING INFORMATION

These highlights do not include all the information needed to use Sodium Fluoride F 18 Injection safely and effectively. See full prescribing information for Sodium Fluoride F 18 Injection.
SODIUM FLUORIDE F 18 INJECTION
For Intravenous Use
Initial U.S. Approval: 1/2011

1 INDICATIONS AND USAGE

Sodium Fluoride F 18 Injection is a radioactive diagnostic agent for positron emission tomography (PET) indicated for imaging of bone to define areas of altered osteogenic activity (1).

2 DOSAGE AND ADMINISTRATION

- Sodium Fluoride F18 Injection emits radiation and must be handled with appropriate safety measures (2.1).
- Administer 300-450 MBq (8 to 12 mCi) as an intravenous injection in adults (2.4).
- Administer approximately 2.1 MBq/kg in children with a minimum of 19 MBq (0.5 mCi) and a maximum of 148 MBq (4 mCi) as an intravenous injection (2.5).
- Imaging can begin 1–2 hours after administration; optimally at one hour post administration (2.7).
- Encourage patients to void immediately prior to imaging the lumbar spine and bony pelvis (2.7).

3 DOSAGE FORMS AND STRENGTHS

Multiple-dose vial containing 370-7,400 MBq/mL (10-200 mCi/mL) at EOS reference time of no-carrier-added sodium fluoride F18 in aqueous 0.9% sodium chloride solution (3). Sodium Fluoride F 18 Injection is a clear, colorless, sterile, pyrogen-free and preservative-free solution for intravenous administration.

4 CONTRAINDICATIONS

None (4).

5 WARNINGS AND PRECAUTIONS

- Allergic Reactions: As with any injectable drug product, allergic reactions and anaphylaxis may occur. Emergency resuscitation equipment and personnel should be immediately available. (5.1).
- Cancer Risk: Sodium Fluoride F 18 Injection may increase the risk of cancer. Use the smallest dose necessary for imaging and ensure safe handling to protect the patient and health care worker (5.2).

(5).

6 ADVERSE REACTIONS

No adverse reactions have been reported for Sodium Fluoride F 18 Injection based on a review of the published literature, publicly available reference sources, and adverse drug reaction reporting systems (6).

To report SUSPECTED ADVERSE REACTIONS, contact 3D Imaging at 1-501-526-5550 or FDA at 1-800-FDA-1088 or www.fda.gov/medwatch.

8 USE IN SPECIFIC POPULATIONS

- Pregnancy: No human or animal data. Any radiopharmaceutical, including Sodium Fluoride F18 injection, may cause fetal harm. Use only if clearly needed (8.1)
- Nursing: A decision should be made whether to interrupt nursing after Sodium Fluoride F 18 Injection administration or not to administer Sodium Fluoride F 18 Injection taking into consideration the importance of the drug to the mother. (8.3).
- Pediatrics: Children are more sensitive to radiation and may be at higher risk of cancer from Sodium Fluoride F18 injection (8.4).

FULL PRESCRIBING INFORMATION

1 INDICATIONS AND USAGE

Sodium Fluoride F 18 Injection is indicated for diagnostic positron emission tomography (PET) imaging of bone to define areas of altered osteogenic activity.

2 DOSAGE AND ADMINISTRATION

2.1 Radiation Safety - Drug Handling

- Wear waterproof gloves and effective shielding when handling Sodium Fluoride F 18 Injection. Use appropriate safety measures, including shielding, consistent with proper patient management to avoid unnecessary radiation exposure to the patient, occupational workers, clinical personnel, and other persons.
- Radiopharmaceuticals should be used by or under the control of physicians who are qualified by specific training and experience in the safe use and handling of radionuclides, and whose experience and training have been approved by the appropriate governmental agency authorized to license the use of radionuclides.
- Use aseptic technique to maintain sterility during all operations involved in the manipulation and administration of Sodium Fluoride F 18 Injection.
- The dose of Sodium Fluoride F 18 Injection should be minimized consistent with the objectives of the procedure, and the nature of the radiation detection devices employed.
- The final dose for the patient should be calculated using proper decay factors from the time of EOS, and measured by a suitable radioactivity calibration system before administration [ Description (11.2)].

2.2 Radiation Safety - Patient Preparation

- To minimize the radiation-absorbed dose to the bladder, encourage adequate hydration. Encourage the patient to ingest at least 500 mL of fluid immediately prior and subsequent to the administration of Sodium Fluoride F 18 Injection.
- Encourage the patient to void one-half hour after administration of Sodium Fluoride F 18 Injection and as frequently thereafter as possible for the next 12 hours.

2.3 Drug Preparation and Administration

- Calculate the necessary volume to administer based on calibration time and dose.
- Inspect Sodium Fluoride F 18 Injection visually for particulate matter and discoloration before administration, whenever solution and container permit.
- Do not administer Sodium Fluoride F 18 Injection containing particulate matter or discoloration; dispose of these unacceptable or unused preparations in a safe manner, in compliance with applicable regulations.
- Aseptically withdraw Sodium Fluoride F 18 Injection from its container.

2.4 Recommended Dose for Adults

Administer 300–450 MBq (8–12 mCi) as an intravenous injection.

2.5 Recommended Dose for Pediatric Patients

In reported clinical experience in approximately 100 children, weight based doses (2.1 MBq/kg) ranging from 19 MBq– 148 MBq (0.5 mCi- 4 mCi) were used.

2.6 Radiation Dosimetry

The age/weight- based estimated absorbed radiation doses (mGy/MBq) from intravenous injection of Sodium Fluoride F 18 Injection are shown in Table 1. These estimates were calculated based on human data and using the data published by the Nuclear Regulatory Commission [1] and the International Commission on Radiological Protection for Sodium Fluoride Injection [2]. The bone, bone marrow and urinary bladder are considered target and critical organs.

Table 1: Estimated Absorbed Radiation Doses after Intravenous Administration of Sodium Fluoride F 18 Injection
 |  |  | Estimated Radiation Dose mGy/MBq
Organ | Adult 70 kg [Data from Nuclear Regulatory Commission Report, Radiation Dose Estimates for Radiopharmaceuticals, NUREG/CR-6345, page 10, 1996.] | 15 year 56.8 kg [Data from ICRP publication 53, Radiation Dose to Patients from Radiopharmaceuticals (), Ann ICRP, Volume 18, , pages15 and 74, 1987] | 10 year 33.2 kg | 5 year 19.8 kg | 1 year 9.7 kg
Adrenals | 0.0062 | 0.012 | 0.018 | 0.028 | 0.052
Brain | 0.0056 | N/A | N/A | N/A | N/A
Bone surfaces | 0.060 | 0.050 | 0.079 | 0.13 | 0.30
Breasts | 0.0028 | 0.0061 | 0.0097 | 0.015 | 0.030
Gallbladder wall | 0.0044 | N/A | N/A | N/A | N/A
Stomach wall | 0.0038 | 0.008 | 0.013 | 0.019 | 0.036
Small intestine | 0.0066 | 0.012 | 0.018 | 0.028 | 0.052
Upper large intestine wall | 0.0058 | 0.010 | 0.016 | 0.026 | 0.046
Lower large intestine wall | 0.012 | 0.016 | 0.025 | 0.037 | 0.063
Heart wall | 0.0039 | N/A | N/A | N/A | N/A
Kidneys | 0.019 | 0.025 | 0.036 | 0.053 | 0.097
Liver | 0.0040 | 0.0084 | 0.013 | 0.021 | 0.039
Lungs | 0.0041 | 0.0084 | 0.013 | 0.020 | 0.039
Muscle | 0.0060 | N/A | N/A | N/A | N/A
Ovaries | 0.011 | 0.016 | 0.023 | 0.036 | 0.063
Pancreas | 0.0048 | 0.0096 | 0.015 | 0.023 | 0.044
Red marrow | 0.028 | 0.053 | 0.088 | 0.18 | 0.38
Skin | 0.0040 | N/A | N/A | N/A | N/A
Spleen | 0.0042 | 0.0088 | 0.014 | 0.021 | 0.041
Testes | 0.0078 | 0.013 | 0.021 | 0.033 | 0.062
Thymus | 0.0035 | N/A | N/A | N/A | N/A
Thyroid | 0.0044 | 0.0084 | 0.013 | 0.020 | 0.036
Urinary bladder wall | 0.25 | 0.27 | 0.4 | 0.61 | 1.1
Uterus | 0.019 | 0.023 | 0.037 | 0.057 | 0.099
Other tissue | N/A | 0.010 | 0.015 | 0.024 | 0.044
Effective Dose Equivalent mSv/MBq | 0.027 | 0.034 | 0.052 | 0.086 | 0.17

2.7 Imaging Guidelines

- Imaging of Sodium Fluoride F 18 Injection can begin 1–2 hours after administration; optimally at 1 hour post administration.
- Encourage the patient to void immediately prior to imaging the fluoride F18 radioactivity in the lumbar spine or bony pelvis.

3 DOSAGE FORMS AND STRENGTHS

Multiple-dose vial containing 370-7,400 MBq/mL (10-200 mCi/mL) at EOS reference time of no-carrier-added sodium fluoride F18 in aqueous 0.9% sodium chloride solution. Sodium Fluoride F 18 Injection is a clear, colorless, sterile, pyrogen-free and preservative-free solution for intravenous administration.

4 CONTRAINDICATIONS

None.

5 WARNINGS AND PRECAUTIONS

5.1 Allergic Reactions

As with any injectable drug product, allergic reactions and anaphylaxis may occur. Emergency resuscitation equipment and personnel should be immediately available.

5.2 Radiation Risks

Sodium Fluoride F 18 Injection may increase the risk of cancer. Carcinogenic and mutagenic studies with Sodium Fluoride F18 injection have not been performed. Use the smallest dose necessary for imaging and ensure safe handling to protect the patient and health care worker [ see Dosage and Administration (2.1)].

6 ADVERSE REACTIONS

No adverse reactions have been reported for Sodium Fluoride F 18 Injection based on a review of the published literature, publicly available reference sources, and adverse drug reaction reporting systems. However, the completeness of these sources is not known.

7 DRUG INTERACTIONS

The possibility of interactions of Sodium Fluoride F 18 Injection with other drugs taken by patients undergoing PET imaging has not been studied.

8 USE IN SPECIFIC POPULATIONS

8.1 Pregnancy

Pregnancy Category C
Any radiopharmaceutical including Sodium Fluoride F18 Injection has a potential to cause fetal harm. The likelihood of fetal harm depends on the stage of fetal development, and the radionuclide dose. Animal reproduction studies have not been conducted with Sodium Fluoride F 18 Injection. Prior to the administration of Sodium Fluoride F 18 Injection to women of childbearing potential, assess for presence of pregnancy. Sodium Fluoride F 18 Injection should be given to a pregnant woman only if clearly needed.

8.3 Nursing Mothers

It is not known whether Sodium Fluoride F 18 Injection is excreted into human milk. Because many drugs are excreted in human milk and because of the potential for serious adverse reactions in nursing infants, a decision should be made whether to interrupt nursing after administration of Sodium Fluoride F 18 Injection or not to administer Sodium Fluoride F 18 Injection, taking into account the importance of the drug to the mother. The body of scientific information related to radioactivity decay, drug tissue distribution and drug elimination shows that less than 0.01% of the radioactivity administered remains in the body after 24 hours (10 half-lives). To minimize the risks to a nursing infant, interrupt nursing for at least 24 hours.

8.4 Pediatric Use

In reported clinical experience in approximately 100 children, weight based doses (2.1 MBq/kg) ranging from 19 MBq – 148 MBq (0.5 mCi - 4 mCi) were used. Sodium Fluoride F18 was shown to localize to areas of bone turnover including rapidly growing epiphyses in developing long bones. Children are more sensitive to radiation and may be at higher risk of cancer from Sodium Fluoride F18 injection.

11 DESCRIPTION

11.1 Chemical Characteristics

Sodium Fluoride F 18 Injection is a positron emitting radiopharmaceutical, containing no-carrier-added, radioactive fluoride F18 that is used for diagnostic purposes in conjunction with PET imaging. It is administered by intravenous injection. The active ingredient, sodium fluoride F18, has the molecular formula Na[^18F] with a molecular weight of 40.99, and has the following chemical structure:

Sodium Fluoride F 18 Injection is provided as a ready-to-use, isotonic, sterile, pyrogen-free, preservative-free, clear and colorless solution. Each mL of the solution contains between 370 MBq to 7,400 MBq (10 mCi to 200 mCi) sodium fluoride F18, at the EOS reference time, in 0.9% aqueous sodium chloride. The pH of the solution is between 4.5 and 8. The solution is presented in 10 mL multiple- dose glass vials with variable total volume and total radioactivity in each container.

11.2 Physical Characteristics

Fluoride F18 decays by positron (β+) emission and has a half-life of 109.7 minutes. Ninety-seven percent of the decay results in emission of a positron with a maximum energy of 633 keV and 3% of the decay results in electron capture with subsequent emission of characteristic X-rays of oxygen. The principal photons useful for diagnostic imaging are the 511 keV gamma photons, resulting from the interaction of the emitted positron with an electron (Table 2). Fluorine F18 atom decays to stable^18O-oxygen.

Table 2: Principal Emission Data for Fluoride F18
Radiation/Emission | % per Disintegration | Mean Energy
Positron (β+) | 96.73 | 249.8 keV
Gamma (±) [Produced by positron annihilation [3] Kocher, D.C. Radioactive Decay Data Tables DOE/TIC-11026, 69, 1981.] | 193.46 | 511.0 keV

The specific gamma ray constant (point source air kerma coefficient) for fluoride F18 is 5.7 R/hr/mCi (1.35 x 10^-6Gy/hr/kBq) at 1 cm. The half-value layer (HVL) for the 511 keV photons is 4 mm lead (Pb). A range of values for the attenuation of radiation results from the interposition of various thickness of Pb. The range of attenuation coefficients for this radionuclide is shown in Table 3. For example, the interposition of an 8 mm thickness of Pb with a coefficient of attenuation of 0.25 will decrease the external radiation by 75%.

Table 3:Radiation Attenuation of 511 keV Photons by Lead (Pb) Shielding
Shield Thickness (Pb) mm | Coefficient of Attenuation
0 | 0.00
4 | 0.50
8 | 0.25
13 | 0.10
26 | 0.01
39 | 0.001
52 | 0.0001

Table 4 lists the fraction of radioactivity remaining at selected time intervals from the calibration time. This information may be used to correct for physical decay of the radionuclide.

Table 4: Physical Decay Chart for Fluoride F18
Time Since Calibration | Fraction Remaining
0 [Calibration time] | 1.00
15 minutes | 0.909
30 minutes | 0.826
60 minutes | 0.683
110 minutes | 0.500
220 minutes | 0.250
440 minutes | 0.060
12 hours | 0.011
24 hours | 0.0001

12 CLINICAL PHARMACOLOGY

12.1 Mechanism of Action

Fluoride F18 ion normally accumulates in the skeleton in an even fashion, with greater deposition in the axial skeleton (e.g. vertebrae and pelvis) than in the appendicular skeleton and greater deposition in the bones around joints than in the shafts of long bones.

12.2 Pharmacodynamics

Increased fluoride F18 ion deposition in bone can occur in areas of increased osteogenic activity during growth, infection, malignancy (primary or metastatic) following trauma, or inflammation of bone.

12.3 Pharmacokinetics

After intravenous administration, fluoride F18 ion is rapidly cleared from the plasma in a biexponential manner. The first phase has a half-life of 0.4 h, and the second phase has a half-life of 2.6 h. Essentially all the fluoride F18 that is delivered to bone by the blood is retained in the bone. One hour after administration of fluoride F18 only about 10% of the injected dose remains in the blood. Fluoride F18 diffuses through capillaries into bone extracellular fluid space, where it becomes bound by chemisorption at the surface of bone crystals, preferentially at sites of newly mineralizing bone.

Deposition of fluoride F18 in bone appears to be primarily a function of blood flow to the bone and the efficiency of the bone in extracting the fluoride F18. Fluoride F18 does not appear to be bound to serum proteins.

In patients with normal renal function, 20% or more of the fluorine ion is cleared from the body in the urine within the first 2 hours after intravenous administration.

13 NONCLINICAL TOXICOLOGY

13.1 Carcinogenesis, Mutagenesis, Impairment of Fertility

Studies to assess reproductive toxicity, mutagenesis and carcinogenesis potential of Sodium Fluoride F 18 Injection have not been performed.

14 CLINICAL STUDIES

14.1 Metastatic Bone Disease

The doses used in reported studies ranged from 2.7 mCi to 20 mCi (100 MBq to 740 MBq), with an average median dose of 10 mCi (370 MBq) and an average mean dose of 9.2 mCi (340 MBq). In PET imaging of bone metastases with Sodium Fluoride F 18 Injection, focally increased tracer uptake is seen in both osteolytic and osteoblastic bone lesions. Negative PET imaging results with Sodium Fluoride F 18 Injection do not preclude the diagnosis of bone metastases. Also, as benign bone lesions are also detected by Sodium Fluoride F 18 Injection, positive PET imaging results cannot replace biopsy to confirm a diagnosis of cancer.

14.2 Other Bone Disorders

The doses used in reported studies ranged from 2.43 mCi to 15 mCi (90 MBq to 555 MBq), with an average median dose of 8.0 mCi (300 MBq) and an average mean dose of 7.6 mCi (280 MBq).

15 REFERENCES

1. Stabin, M.G., Stubbs, J.B. and Toohey R.E., Radiation Dose Estimates for Radiopharmaceuticals,U.S. Nuclear Regulatory Commission report NUREG/CR-6345, page 10, 1996.
2. Radiation Dose to Patients from Radiopharmaceuticals,ICRP publication 53, Ann ICRP, 18 pages 15 and 74, 1987.
3. Kocher, D.C., "Radioactive Decay Data Tables: A Handbook of decay data for application to radiation dosimetry and radiological assessments" DOE/TIC-11026, page 69, 1981.

16 HOW SUPPLIED

Sodium Fluoride F 18 Injection is supplied in a multiple-dose Type I glass vial with (elastomeric) stopper and aluminum crimp seal containing between 370-7,400 MBq/mL (10 to 200 mCi/mL) of no-carrier-added sodium fluoride F18, at the EOS reference time, in aqueous 0.9% sodium chloride solution. The total volume and total radioactivity per vial are variable. Each vial is enclosed in a shielding container of appropriate thickness.

The product is available in a 10 mL vial configuration with a variable fill volume. The NDC numbers are:
76451-018-10 (10 mL vial)

Storage

Store at 25°C (77°F); excursions permitted to 15–30°C (59–86°F). Use the solution within 12 hours of the EOS reference time.

Handling

Receipt, transfer, handling, possession, or use of this product is subject to the radioactive material regulations and licensing requirements of the U.S. Nuclear Regulatory Commission, Agreement States or Licensing States as appropriate.

17 PATIENT COUNSELING INFORMATION

17.1 Pre-study Hydration

Encourage patients to drink at least 500 mL of water prior to drug administration.

17.2 Post-study Voiding

To help protect themselves and others in their environment, patients should take the following precautions for 12 hours after injection: whenever possible, use a toilet and flush several times after each use; wash hands thoroughly after each voiding or fecal elimination. If blood, urine or feces soil clothing, wash the clothing separately.

Manufactured by:
3D Imaging Drug Design and Development LLC
PO Box 13267
Maumelle, AR 72113-6657

Distributed by:
3D Imaging Drug Design and Development LLC
PO Box 13267
Maumelle, AR 72113-6657

PACKAGE INNER AND OUTER LABELS

Outer labels are exterior to the radiation shielding for the product vial and contain the direct labeling information. There is an inner label that can be printed and applied in advance to avoid radiation dose to the operators and is small enough to affix to the vial. The inner label contains the product name and a batch number that positively connects it to the correct outer label. The outer label contains complete package label information and all dose information that is determined at the time of filling.